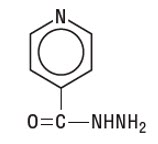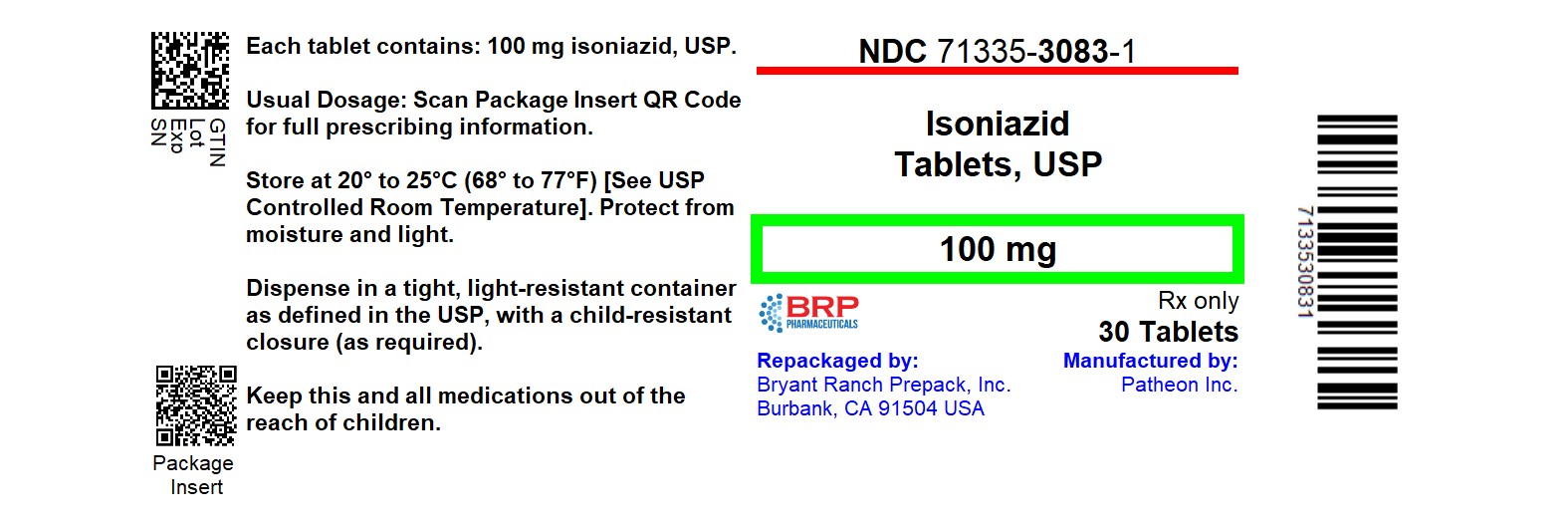 DRUG LABEL: Isoniazid
NDC: 71335-3083 | Form: TABLET
Manufacturer: Bryant Ranch Prepack
Category: prescription | Type: HUMAN PRESCRIPTION DRUG LABEL
Date: 20260216

ACTIVE INGREDIENTS: ISONIAZID 100 mg/1 1
INACTIVE INGREDIENTS: SILICON DIOXIDE; CROSPOVIDONE (120 .MU.M); MICROCRYSTALLINE CELLULOSE; STARCH, CORN; TALC

Isoniazid Tablets, USP

WARNING

Severe and sometimes fatal hepatitis associated with isoniazid therapy has been reported and may occur or may develop even after many months of treatment. The risk of developing hepatitis is age related. Approximate case rates by age are: less than 1 per 1,000 for persons under 20 years of age, 3 per 1,000 for persons in the 20 to 34 year age group, 12 per 1,000 for persons in the 35 to 49 year age group, 23 per 1,000 for persons in the 50 to 64 year age group and 8 per 1,000 for persons over 65 years of age. The risk of hepatitis is increased with daily consumption of alcohol. Precise data to provide a fatality rate for isoniazid-related hepatitis is not available; however, in a U.S. Public Health Service Surveillance Study of 13,838 persons taking isoniazid, there were 8 deaths among 174 cases of hepatitis.

Therefore, patients given isoniazid should be carefully monitored and interviewed at monthly intervals. For persons 35 and older, in addition to monthly symptom reviews, hepatic enzymes (specifically, AST and ALT [formerly SGOT and SGPT, respectively]) should be measured prior to starting isoniazid therapy and periodically throughout treatment. Isoniazid-associated hepatitis usually occurs during the first three months of treatment. Usually, enzyme levels return to normal despite continuance of drug, but in some cases progressive liver dysfunction occurs. Other factors associated with an increased risk of hepatitis include daily use of alcohol, chronic liver disease and injection drug use. A recent report suggests an increased risk of fatal hepatitis associated with isoniazid among women, particularly black and Hispanic women. The risk may also be increased during the post partum period. More careful monitoring should be considered in these groups, possibly including more frequent laboratory monitoring. If abnormalities of liver function exceed three to five times the upper limit of normal, discontinuation of isoniazid should be strongly considered. Liver function tests are not a substitute for a clinical evaluation at monthly intervals or for the prompt assessment of signs or symptoms of adverse reactions occurring between regularly scheduled evaluations. Patients should be instructed to immediately report signs or symptoms consistent with liver damage or other adverse effects. These include any of the following: unexplained anorexia, nausea, vomiting, dark urine, icterus, rash, persistent paresthesias of the hands and feet, persistent fatigue, weakness or fever of greater than 3 days duration and/or abdominal tenderness, especially right upper quadrant discomfort. If these symptoms appear or if signs suggestive of hepatic damage are detected, isoniazid should be discontinued promptly, since continued use of the drug in these cases has been reported to cause a more severe form of liver damage.

Patients with tuberculosis who have hepatitis attributed to isoniazid should be given appropriate treatment with alternative drugs. If isoniazid must be reinstituted, it should be reinstituted only after symptoms and laboratory abnormalities have cleared. The drug should be restarted in very small and gradually increasing doses and should be withdrawn immediately if there is any indication of recurrent liver involvement.

Preventive treatment should be deferred in persons with acute hepatic diseases.

DESCRIPTION

Isoniazid, USP is an antibacterial available as 100 mg and 300 mg tablets for oral administration. Each tablet also contains as inactive ingredients: colloidal silicon dioxide, crospovidone, hydrogenated vegetable oil, microcrystalline cellulose, pregelatinized corn starch and talc.

Isoniazid, USP is chemically known as isonicotinyl hydrazine or isonicotinic acid hydrazide. It has the following structural formula:

C6H7N3O

M.W. 137.14

Isoniazid, USP is odorless, and occurs as a colorless or white crystalline powder or as white crystals. It is freely soluble in water, sparingly soluble in alcohol and slightly soluble in chloroform and in ether. Isoniazid, USP is slowly affected by exposure to air and light.

CLINICAL PHARMACOLOGY

Within 1 to 2 hours after oral administration, isoniazid produces peak blood levels which decline to 50 percent or less within 6 hours. It diffuses readily into all body fluids (cerebrospinal, pleural and ascitic fluids), tissues, organs and excreta (saliva, sputum and feces). The drug also passes through the placental barrier and into milk in concentrations comparable to those in the plasma. From 50 to 70 percent of a dose of isoniazid is excreted in the urine in 24 hours.

Isoniazid is metabolized primarily by acetylation and dehydrazination. The rate of acetylation is genetically determined. Approximately 50 percent of Blacks and Caucasians are "slow inactivators" and the rest are "rapid inactivators"; the majority of Eskimos and Orientals are rapid inactivators."

The rate of acetylation does not significantly alter the effectiveness of isoniazid. However, slow acetylation may lead to higher blood levels of the drug and, thus, to an increase in toxic reactions.

Pyridoxine (vitamin B6) deficiency is sometimes observed in adults with high doses of isoniazid and is considered probably due to its competition with pyridoxal phosphate for the enzyme apotryptophanase.

Mechanism of Action

Isoniazid inhibits the synthesis of mycoloic acids, an essential component of the bacterial cell wall. At therapeutic levels isoniazid is bactericidal against actively growing intracellular and extracellular Mycobacterium tuberculosis organisms.

Resistance

Resistance to isoniazid occurs because of mutations in the katG, inhA, kasA and ahpC genes. Resistance in M. tuberculosis develops rapidly when isoniazid monotherapy is administered.

Susceptibility Testing

For specific information regarding susceptibility test criteria and associated test methods and quality control standards recognized by FDA for this drug, please see: www.fda.gov/STIC.

INDICATIONS AND USAGE

Isoniazid tablets, USP are recommended for all forms of tuberculosis in which organisms are susceptible. However, active tuberculosis must be treated with multiple concomitant anti-tuberculosis medications to prevent the emergence of drug resistance. Single-drug treatment of active tuberculosis with isoniazid or any other medication, is inadequate therapy.

Isoniazid tablets, USP are recommended as preventive therapy for the following groups, regardless of age. (Note: the criterion for a positive reaction to a skin test (in millimeters of induration) for each group is given in parenthesis):

1. Persons with human immunodeficiency virus (HIV) infection (greater than or equal to 5 mm) and persons with risk factors for HIV infection whose HIV infection status is unknown but who are suspected of having HIV infection. Preventive therapy may be considered for HIV infected persons who are tuberculin-negative but belong to groups in which the prevalence of tuberculosis infection is high. Candidates for preventive therapy who have HIV infection should have a minimum of 12 months of therapy.
2. Close contacts of persons with newly diagnosed infectious tuberculosis (greater than or equal to 5 mm). In addition, tuberculin-negative (less than 5 mm) children and adolescents who have been close contacts of infectious persons within the past 3 months are candidates for preventive therapy until a repeat tuberculin skin test is done 12 weeks after contact with the infectious source. If the repeat skin test is positive (greater than 5mm), therapy should be continued.
3. Recent converters, as indicated by a tuberculin skin test (greater than or equal to 10 mm increase within a 2-year period for those less than 35 years old; greater than or equal to 15 mm increase for those greater than or equal to 35 years of age). All infants and children younger than 4 years of age with a greater than 10 mm skin test are included in this category.
4. Persons with abnormal chest radiographs that show fibrotic lesions likely to represent old healed tuberculosis (greater than or equal to 5 mm). Candidates for preventive therapy who have fibrotic pulmonary lesions consistent with healed tuberculosis or who have pulmonary silicosis should have 12 months of isoniazid or 4 months of isoniazid and rifampin, concomitantly.
5. Intravenous drug users known to be HIV-seronegative (greater than 10 mm).
6. Persons with the following medical conditions that have been reported to increase the risk of tuberculosis (greater than or equal to 10 mm): silicosis; diabetes mellitus; prolonged therapy with adrenocorticosteroids; immunosuppressive therapy; some hematologic and reticuloendothelial diseases, such as leukemia or Hodgkin's disease; end-stage renal disease; clinical situations associated with substantial rapid weight loss or chronic undernutrition (including: intestinal bypass surgery for obesity, the postgastrectomy state [with or without weight loss], chronic peptic ulcer disease, chronic malabsorption syndromes and carcinomas of the oropharynx and upper gastrointestinal tract that prevent adequate nutritional intake). Candidates for preventive therapy who have fibrotic pulmonary lesions consistent with healed tuberculosis or who have pulmonary silicosis should have 12 months of isoniazid or 4 months of isoniazid and rifampin, concomitantly.

Additionally, in the absence of any of the above risk factors, persons under the age of 35 with a tuberculin skin test reaction of 10 mm or more are also appropriate candidates for preventive therapy if they are a member of any of the following high-incidence groups:

1. Foreign-born persons from high-prevalence countries who never received BCG vaccine.
2. Medically underserved low-income populations, including high-risk racial or ethnic minority populations, especially blacks, Hispanics and Native Americans.
3. Residents of facilities for long-term care (e.g., correctional institutions, nursing homes and mental institutions).

Children who are less than 4 years old are candidates for isoniazid preventive therapy if they have greater than 10 mm induration from a PPD Mantoux tuberculin skin test.

Finally, persons under the age of 35 who a) have none of the above risk factors (1 to 6); b) belong to none of the high-incidence groups; and c) have a tuberculin skin test reaction of 15 mm or more, are appropriate candidates for preventive therapy.

The risk of hepatitis must be weighed against the risk of tuberculosis in positive tuberculin reactors over the age of 35. However, the use of isoniazid is recommended for those with the additional risk factors listed above (1 to 6) and on an individual basis in situations where there is likelihood of serious consequences to contacts who may become infected.

CONTRAINDICATIONS

Isoniazid is contraindicated in patients who develop severe hypersensitivity reactions, including drug-induced hepatitis; previous isoniazid-associated hepatic injury; severe adverse reactions to isoniazid such as drug fever, chills, arthritis; and acute liver disease of any etiology.

WARNINGS

See the boxed warning.

Severe cutaneous adverse reactions (SCARs) including toxic epidermal necrolysis (TEN), Stevens-Johnson syndrome (SJS), drug reaction with eosinophilia and systemic symptoms (DRESS), and acute generalized exanthematous pustulosis (AGEP) have been reported with the use of isoniazid (see ADVERSE REACTIONS). Symptoms can be serious and potentially life threatening. If symptoms or signs of SCARs develop, discontinue isoniazid tablets immediately and institute appropriate therapy.

Cerebellar Syndrome

Cerebellar syndrome which may include abnormal motor coordination presenting as gait, trunk, and limb ataxia, dysmetria and dysdiadochokinesia, intention tremor, dysarthria, or nystagmus, has been reported in postmarketing case reports with the use of isoniazid (see ADVERSE REACTIONS). Most cases of cerebellar syndrome involved patients with chronic kidney disease (CKD), however, cerebellar syndrome was also reported in patients without CKD. Discontinue isoniazid tablets if symptoms or signs of cerebellar syndrome occur.

PRECAUTIONS

General

All drugs should be stopped and an evaluation made at the first sign of a hypersensitivity reaction. If isoniazid therapy must be reinstituted, the drug should be given only after symptoms have cleared. The drug should be restarted in very small and gradually increasing doses and should be withdrawn immediately if there is any indication of recurrent hypersensitivity reaction.

Use of isoniazid should be carefully monitored in the following:

1. Daily users of alcohol. Daily ingestion of alcohol may be associated with a higher incidence of + isoniazid hepatitis.
2. Patients with active chronic liver disease or severe renal dysfunction.
3. Age greater than 35.
4. Concurrent use of any chronically administered medication.
5. History of previous discontinuation of isoniazid.
6. Existence of peripheral neuropathy or conditions predisposing to neuropathy.
7. Pregnancy.
8. Injection drug use.
9. Women belonging to minority groups, particularly in the postpartum period.
10. HIV seropositive patients.

Laboratory Tests

Because there is a higher frequency of isoniazid associated hepatitis among certain patient groups, including Age greater than 35, daily users of alcohol, chronic liver disease, injection drug use and women belonging to minority groups, particularly in the post-partum period, transaminase measurements should be obtained prior to starting and monthly during preventative therapy or more frequently as needed. If any of the values exceed three to five times the upper limit of normal, isoniazid should be temporarily discontinued and consideration given to restarting therapy.

Drug Interactions

Food

Isoniazid should not be administered with food. Studies have shown that the bioavailability of isoniazid is reduced significantly when administered with food. Tyramine- and histamine-containing foods should be avoided in patients receiving isoniazid. Because isoniazid has some monoamine oxidase inhibiting activity, an interaction with tyramine-containing foods (cheese, red wine) may occur. Diamine oxidase may also be inhibited, causing exaggerated response (e.g., headache, sweating, palpitations, flushing, hypotension) to foods containing histamine (e.g., skipjack, tuna, other tropical fish).

Acetaminophen

A report of severe acetaminophen toxicity was reported in a patient receiving isoniazid. It is believed that the toxicity may have resulted from a previously unrecognized interaction between isoniazid and acetaminophen and a molecular basis for this interaction has been proposed. However, current evidence suggests that isoniazid does induce P-450IIE1, a mixed-function oxidase enzyme that appears to generate the toxic metabolites, in the liver. Furthermore it has been proposed that isoniazid resulted in induction of P-450IIE1 in the patient's liver which, in turn, resulted in a greater proportion of the ingested acetaminophen being converted to the toxic metabolites. Studies have demonstrated that pretreatment with isoniazid potentiates acetaminophen hepatotoxicity in rats^1,2.

Carbamazepine

Isoniazid is known to slow the metabolism of carbamazepine and increase its serum levels. Carbamazepine levels should be determined prior to concurrent administration with isoniazid, signs and symptoms of carbamazepine toxicity should be monitored closely and appropriate dosage adjustment of the anticonvulsant should be made^3.

Ketoconazole

Potential interaction of ketoconazole and isoniazid may exist. When ketoconazole is given in combination with isoniazid and rifampin the AUC of ketoconazole is decreased by as much as 88 percent after 5 months of concurrent isoniazid and rifampin therapy^4.

Phenytoin

Isoniazid may increase serum levels of phenytoin. To avoid phenytoin intoxication, appropriate adjustment of the anticonvulsant should be made^5,6.

Theophylline

A recent study has shown that concomitant administration of isoniazid and theophylline may cause elevated plasma levels of theophylline and in some instances a slight decrease in the elimination of isoniazid. Since the therapeutic range of theophylline is narrow, theophylline serum levels should be monitored closely and appropriate dosage adjustments of theophylline should be made^7.

Valproate

A recent case study has shown a possible increase in the plasma level of valproate when co-administered with isoniazid. Plasma valproate concentration should be monitored when isoniazid and valproate are co-administered and appropriate dosage adjustments of valproate should be made^5.

Carcinogenesis and Mutagenesis

Isoniazid has been shown to induce pulmonary tumors in a number of strains of mice. Isoniazid has not been shown to be carcinogenic in humans. (Note: a diagnosis of mesothelioma in a child with prenatal exposure to isoniazid and no other apparent risk factors has been reported). Isoniazid has been found to be weakly mutagenic in strains TA 100 and TA 1535 of Salmonella typhimurium (Ames assay) without metabolic activation.

Pregnancy

Teratogenic Effects

Pregnancy Category C

Isoniazid has been shown to have an embryocidal effect in rats and rabbits when given orally during pregnancy. Isoniazid was not teratogenic in reproduction studies in mice, rats and rabbits. There are no adequate and well-controlled studies in pregnant women. Isoniazid should be used as a treatment for active tuberculosis during pregnancy because the benefit justifies the potential risk to the fetus. The benefit of preventive therapy also should be weighed against a possible risk to the fetus. Preventive therapy generally should be started after delivery to prevent putting the fetus at risk of exposure; the low levels of isoniazid in breast milk do not threaten the neonate. Since isoniazid is known to cross the placental barrier, neonates of isoniazid treated mothers should be carefully observed for any evidence of adverse effects.

Nonteratogenic Effects

Since isoniazid is known to cross the placental barrier, neonates of isoniazid-treated mothers should be carefully observed for any evidence of adverse effects.

Nursing Mothers

The small concentrations of isoniazid in breast milk do not produce toxicity in the nursing newborn; therefore, breast feeding should not be discouraged. However, because levels of isoniazid are so low in breast milk, they cannot be relied upon for prophylaxis or therapy of nursing infants.

ADVERSE REACTIONS

The most frequent reactions are those affecting the nervous system and the liver.

Nervous System Reactions

Peripheral neuropathy is the most common toxic effect. It is dose-related, occurs most often in the malnourished and in those predisposed to neuritis (e.g., alcoholics and diabetics) and is usually preceded by paresthesias of the feet and hands. The incidence is higher in "slow inactivators".

Other neurotoxic effects, which are uncommon with conventional doses, are convulsions, toxic encephalopathy, optic neuritis and atrophy, memory impairment and toxic psychosis.

Cerebellar syndrome, which may include abnormal motor coordination manifesting as gait, trunk, and limb ataxia, dysmetria and dysdiadochokinesia, intention tremor, dysarthria, or nystagmus, have been reported in post marketing case reports (see WARNINGS).

Hepatic Reactions

See boxed warning. Elevated serum transaminase (SGOT; SGPT), bilirubinemia, bilirubinuria, jaundice and occasionally severe and sometimes fatal hepatitis. The common prodromal symptoms of hepatitis are anorexia, nausea, vomiting, fatigue, malaise and weakness. Mild hepatic dysfunction, evidenced by mild and transient elevation of serum transaminase levels occurs in 10 to 20 percent of patients taking isoniazid. This abnormality usually appears in the first 1 to 3 months of treatment but can occur at any time during therapy. In most instances, enzyme levels return to normal and generally, there is no necessity to discontinue medication during the period of mild serum transaminase elevation. In occasional instances, progressive liver damage occurs, with accompanying symptoms. If the SGOT value exceeds three to five times the upper limit of normal, discontinuation of the isoniazid should be strongly considered. The frequency of progressive liver damage increases with age. It is rare in persons under 20, but occurs in up to 2.3 percent of those over 50 years of age.

Gastrointestinal Reactions

Nausea, vomiting, epigastric distress, and pancreatitis.

Hematologic Reactions

Agranulocytosis; hemolytic, sideroblastic or aplastic anemia, thrombocytopenia; and eosinophilia.

Hypersensitivity Reactions

Fever, skin eruptions (morbilliform, maculopapular, purpuric or exfoliative), lymphadenopathy, vasculitis, acute generalized exanthematous pustulosis (AGEP), Stevens-Johnson syndrome (SJS), toxic epidermal necrolysis, and drug reaction with eosinophilia syndrome (DRESS) (see WARNINGS).

Metabolic and Endocrine Reactions

Pyridoxine deficiency, pellagra, hyperglycemia, metabolic acidosis and gynecomastia.

Miscellaneous Reactions

Rheumatic syndrome and systemic lupus erythematosus-like syndrome.

OVERDOSAGE

Signs and Symptoms

Isoniazid overdosage produces signs and symptoms within 30 minutes to 3 hours after ingestion. Nausea, vomiting, dizziness, slurring of speech, blurring of vision and visual hallucinations (including bright colors and strange designs) are among the early manifestations. With marked overdosage, respiratory distress and CNS depression, progressing rapidly from stupor to profound coma, are to be expected, along with severe, intractable seizures. Severe metabolic acidosis, acetonuria and hyperglycemia are typical laboratory findings.

Treatment

Untreated or inadequately treated cases of gross isoniazid overdosage, 80 mg/kg to 150 mg/kg, can cause neurotoxicity6 and terminate fatally, but good response has been reported in most patients brought under adequate treatment within the first few hours after drug ingestion.

For the Asymptomatic Patient

Absorption of drugs from the GI tract may be decreased by giving activated charcoal. Gastric emptying should also be employed in the asymptomatic patient. Safeguard the patient's airway when employing these procedures. Patients who acutely ingest greater than 80 mg/kg should be treated with intravenous pyridoxine on a gram per gram basis equal to the isoniazid dose. If an unknown amount of isoniazid is ingested, consider an initial dose of 5 grams of pyridoxine given over 30 to 60 minutes in adults or 80 mg/kg of pyridoxine in children.

For the Symptomatic Patient

Ensure adequate ventilation, support cardiac output and protect the airway while treating seizures and attempting to limit absorption. If the dose of isoniazid is known, the patient should be treated initially with a slow intravenous bolus of pyridoxine, over 3 to 5 minutes, on a gram per gram basis, equal to the isoniazid dose. If the quantity of isoniazid ingestion is unknown, then consider an initial intravenous bolus of pyridoxine of 5 grams in the adult or 80 mg/kg in the child. If seizures continue, the dosage of pyridoxine may be repeated. It would be rare that more than 10 grams of pyridoxine would need to be given. The maximum safe dose for pyridoxine in isoniazid intoxication is not known. If the patient does not respond to pyridoxine, diazepam may be administered. Phenytoin should be used cautiously, because isoniazid interferes with the metabolism of phenytoin.

General

Obtain blood samples for immediate determination of gases, electrolytes, BUN, glucose, etc.; type and cross-match blood in preparation for possible hemodialysis.

Rapid Control of Metabolic Acidosis

Patients with this degree of INH intoxication are likely to have hypoventilation. The administration of sodium bicarbonate under these circumstances can cause exacerbation of hypercarbia. Ventilation must be monitored carefully, by measuring blood carbon dioxide levels and supported mechanically, if there is respiratory insufficiency.

Dialysis

Both peritoneal and hemodialysis have been used in the management of isoniazid overdosage. These procedures are probably not required if control of seizures and acidosis is achieved with pyridoxine, diazepam and bicarbonate.

Along with measures based on initial and repeated determination of blood gases and other laboratory tests as needed, utilize meticulous respiratory and other intensive care to protect against hypoxia, hypotension, aspiration, pneumonitis, etc.

DOSAGE AND ADMINISTRATION

(See also INDICATIONS AND USAGE)

NOTE

For preventive therapy of tuberculous infection and treatment of tuberculosis, it is recommended that physicians be familiar with the following publications: (1) the recommendations of the Advisory Council for the Elimination of Tuberculosis, published in the MMWR: vol 42; RR-4, 1993 and (2) Treatment of Tuberculosis and Tuberculosis Infection in Adults and Children, American Journal of Respiratory and Critical Care Medicine: vol 149; 1359-1374, 1994.

For Treatment of Tuberculosis

Isoniazid is used in conjunction with other effective anti-tuberculous agents. Drug susceptibility testing should be performed on the organisms initially isolated from all patients with newly diagnosed tuberculosis. If the bacilli becomes resistant, therapy must be changed to agents to which the bacilli are susceptible.

Usual Oral Dosage (depending on the regimen used):

Adults

5 mg/kg up to 300 mg daily in a single dose; or
15 mg/kg up to 900 mg/day, two or three times/week

Children

10 mg/kg to 15 mg/kg up to 300 mg daily in a single dose; or
20 mg/kg to 40 mg/kg up to 900 mg/day, two or three times/week

Patients with Pulmonary Tuberculosis Without HIV Infection

There are 3 regimen options for the initial treatment of tuberculosis in children and adults:

Option 1

Daily isoniazid, rifampin and pyrazinamide for 8 weeks followed by 16 weeks of isoniazid and rifampin daily or 2 to 3 times weekly. Ethambutol or streptomycin should be added to the initial regimen until sensitivity to isoniazid and rifampin is demonstrated. The addition of a fourth drug is optional if the relative prevalence of isoniazid-resistant Mycobacterium tuberculosis isolates in the community is less than or equal to four percent.

Option 2

Daily isoniazid, rifampin, pyrazinamide and streptomycin or ethambutol for 2 weeks followed by twice weekly administration of the same drugs for 6 weeks, subsequently twice weekly isoniazid and rifampin for 16 weeks.

Option 3

Three times weekly with isoniazid, rifampin, pyrazinamide and ethambutol or streptomycin for 6 months.

*All regimens given twice weekly or 3 times weekly should be administered by directly observed therapy [see also Directly Observed Therapy (DOT)].

The above treatment guidelines apply only when the disease is caused by organisms that are susceptible to the standard antituberculous agents. Because of the impact of resistance to isoniazid and rifampin on the response to therapy, it is essential that physicians initiating therapy for tuberculosis be familiar with the prevalence of drug resistance in their communities. It is suggested that ethambutol not be used in children whose visual acuity cannot be monitored.

Patients with Pulmonary Tuberculosis and HIV Infection

The response of the immunologically impaired host to treatment may not be as satisfactory as that of a person with normal host responsiveness. For this reason, therapeutic decisions for the impaired host must be individualized. Since patients co-infected with HIV may have problems with malabsorption, screening of antimycobacterial drug levels, especially in patients with advanced HIV disease, may be necessary to prevent the emergence of MDRTB.

Patients with Extra Pulmonary Tuberculosis

The basic principles that underlie the treatment of pulmonary tuberculosis also apply to extra pulmonary forms of the disease. Although there have not been the same kinds of carefully conducted controlled trials of treatment of extra pulmonary tuberculosis as for pulmonary disease, increasing clinical experience indicates that a 6 to 9 month short-course regimen is effective. Because of the insufficient data, miliary tuberculosis, bone/joint tuberculosis and tuberculous meningitis in infants and children should receive 12 month therapy.

Bacteriologic evaluation of extra pulmonary tuberculosis may be limited by the relative inaccessibility of the sites of disease. Thus, response to treatment often must be judged on the basis of clinical and radiographic findings.

The use of adjunctive therapies such as surgery and corticosteroids is more commonly required in extra pulmonary tuberculosis than in pulmonary disease. Surgery may be necessary to obtain specimens for diagnosis and to treat such processes as constrictive pericarditis and spinal cord compression from Pott's Disease. Corticosteroids have been shown to be of benefit in preventing cardiac constriction from tuberculous pericarditis and in decreasing the neurologic sequelae of all stages of tuberculosis meningitis, especially when administered early in the course of the disease.

Pregnant Women with Tuberculosis

The options listed above must be adjusted for the pregnant patient. Streptomycin interferes with in utero development of the ear and may cause congenital deafness. Routine use of pyrazinamide is also not recommended in pregnancy because of inadequate teratogenicity data. The initial treatment regimen should consist of isoniazid and rifampin. Ethambutol should be included unless primary isoniazid resistance is unlikely (isoniazid resistance rate documented to be less than 4%).

Treatment of Patients with Multi-Drug Resistant Tuberculosis (MDRTB)

Multiple-drug resistant tuberculosis (i.e., resistance to at least isoniazid and rifampin) presents difficult treatment problems. Treatment must be individualized and based on susceptibility studies. In such cases, consultation with an expert in tuberculosis is recommended.

Directly Observed Therapy (DOT)

A major cause of drug-resistant tuberculosis is patient noncompliance with treatment. The use of DOT can help assure patient compliance with drug therapy. DOT is the observation of the patient by a health care provider or other responsible person as the patient ingests anti-tuberculosis medications. DOT can be achieved with daily, twice weekly or thrice weekly regimens and is recommended for all patients.

For Preventative Therapy of Tuberculosis

Before isoniazid preventive therapy is initiated, bacteriologically positive or radiographically progressive tuberculosis must be excluded. Appropriate evaluations should be performed if extra pulmonary tuberculosis is suspected.

Adults over 30 kg: 300 mg per day in a single dose.
Infants and Children: 10 mg/kg (up to 300 mg daily) in a single dose.

In situations where adherence with daily preventative therapy cannot be assured, 20 mg/kg to 30 mg/kg (not to exceed 900 mg) twice weekly under the direct observation of a health care worker at the time of administration^8.

Continuous administration of isoniazid for a sufficient period is an essential part of the regimen because relapse rates are higher if chemotherapy is stopped prematurely. In the treatment of tuberculosis, resistant organisms may multiply and the emergence of resistant organisms during the treatment may necessitate a change in the regimen.

For following patient compliance: the Potts-Cozart test^9, a simple colorimetric^6 method of checking for isoniazid in the urine, is a useful tool for assuring patient compliance, which is essential for effective tuberculosis control. Additionally, isoniazid test strips are also available to check patient compliance.

Concomitant administration of pyridoxine (B6) is recommended in the malnourished and in those predisposed to neuropathy (e.g., alcoholics and diabetics).

HOW SUPPLIED

Isoniazid tablets, USP are available as follows:

100 mg: White to off-white, round, scored, flat-faced, beveled-edge tablet, debossed with 01 on one side and G over L on the other side.

- NDC 71335-3083-1: 30 Tablets in a BOTTLE

Protect from moisture and light.

Dispense in a tight, light-resistant container as defined in the USP, with a child-resistant closure (as required).

Store at 20° to 25°C (68° to 77°F) [See USP Controlled Room Temperature].

KEEP THIS AND ALL MEDICATIONS OUT OF THE REACH OF CHILDREN.

Repackaged/Relabeled by:
Bryant Ranch Prepack
Burbank, CA 91504

References

1. Murphy, R., et al: Annuals of Internal Medicine; 1990: November 15; volume 113: 799-800.
2. Burke, R.F., et al: Res Commun Chem Pathol Pharmacol; 1990: July; vol. 69: 115-118.
3. Fleenor, M.F., et al: Chest (United States) Letter; 1991; June; 99 (6): 1554.
4. Baciewicz, A.M. and Baciewicz, Jr. F.A.: Arch Int Med 1993: September; volume 153: 1970-1971.
5. Jonviller, A.P., et al: European Journal of Clinical Pharmacol (Germany), 1991: 40 (2) p198.
6. American Thoracic Society/Centers for Disease Control: Treatment of Tuberculosis and Tuberculosis Infection in Adults and Children. Amer. J. Respir Crit Care Med. 1994; 149: p1359-1374.
7. Hoglund P., et al: European Journal of Respir Dis (Denmark) 1987: February; 70 (2) p110-116.
8. Committee on infectious Diseases American Academy of Pediatrics: 1994, Red Book: Report of the Committee on Infectious Diseases; 23 edition; p487.
9. Schraufnagel, DE; Testing for Isoniazid; Chest (United States) 1990: August; 98 (2) p314-316.

To report SUSPECTED ADVERSE REACTIONS, contact Allucent at 1-866-511-6754 or FDA at 1-800-FDA-1088 or www.fda.gov/medwatch.

Manufactured In Canada By:
Patheon Inc.
Whitby, ON, Canada L1N 5Z5
Manufactured For:
Genus Lifesciences Inc.
Allentown, PA 18102

Rev. 02/2025

PACKAGE LABEL

Isoniazid 100mg Tablets